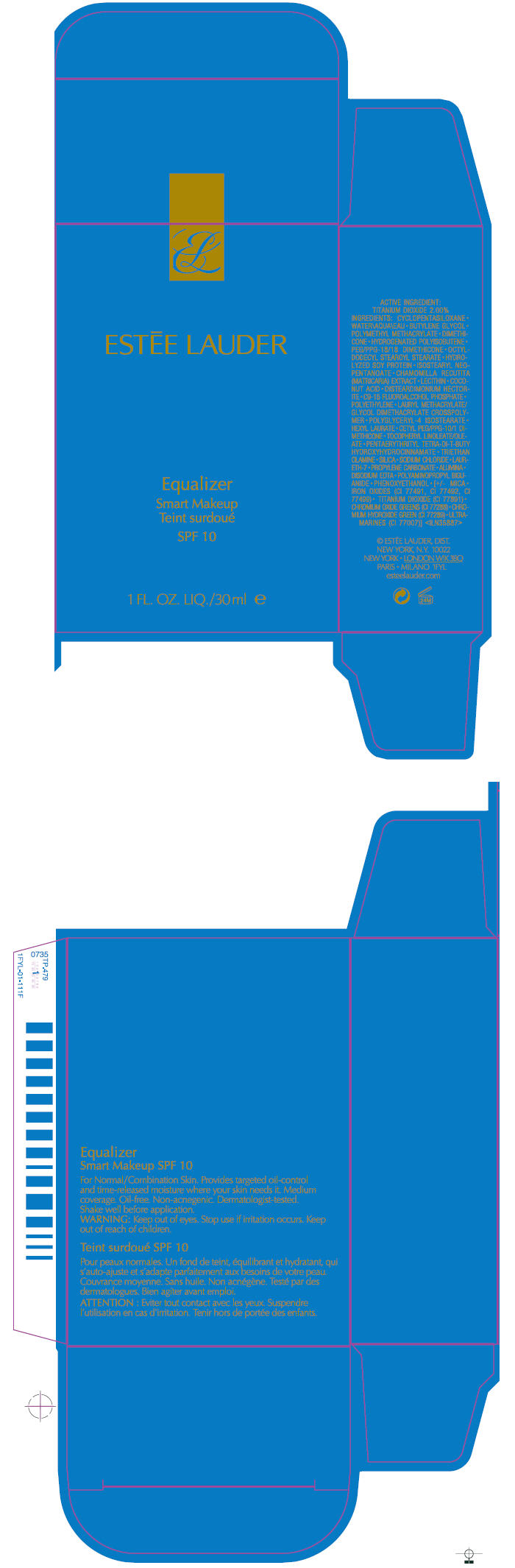 DRUG LABEL: EQUALIZER 
NDC: 11559-736 | Form: LOTION
Manufacturer: Estee Lauder Inc.
Category: otc | Type: HUMAN OTC DRUG LABEL
Date: 20111028

ACTIVE INGREDIENTS: TITANIUM DIOXIDE 2 mL/100 mL
INACTIVE INGREDIENTS: CYCLOMETHICONE 5; WATER; BUTYLENE GLYCOL; DIMETHICONE; HEXYLENE GLYCOL; OCTYLDODECYL STEAROYL STEARATE; MATRICARIA RECUTITA; COCONUT ACID; HIGH DENSITY POLYETHYLENE; POLYGLYCERYL-4 ISOSTEARATE; HEXYL LAURATE; SILICON DIOXIDE; SODIUM CHLORIDE; LAURETH-7; PROPYLENE CARBONATE; ALUMINUM OXIDE; EDETATE DISODIUM; PHENOXYETHANOL; MICA; FERRIC OXIDE RED; FERRIC OXIDE YELLOW; FERROSOFERRIC OXIDE

Equalizer
Smart Makeup

ACTIVE INGREDIENT

TITANIUM DIOXIDE 2.00%

INGREDIENTS

CYCLOPENTASILOXANE • WATER • BUTYLENE GLYCOL • POLYMETHYL METHACRYLATE • DIMETHICONE • ISOTETRACOSANE • HEXYLENE GLYCOL • PEG/PPG-18/18 DIMETHICONE • OCTYLDODECYL STEAROYL STEARATE • HYDROLYZED SOY PROTEIN • ISOSTEARYL NEOPENTANOATE • CHAMOMILLA RECUTITA (MATRICARIA) EXTRACT • LECITHIN • COCONUT ACID • DISTEARDIMONIUM HECTORITE • C9-15 FLUOROALCOHOL PHOSPHATE • POLYETHYLENE • LAURYL METHACRYLATE/GLYCOL DIMETHACRYLATE CROSSPOLYMER • POLYGLYCERYL-4 ISOSTEARATE • HEXYL LAURATE • CETYL PEG/PPG-10/1 DIMETHICONE • TOCOPHERYL LINOLEATE/OLEATE • SILICA • SODIUM CHLORIDE • LAURETH-7 • PROPYLENE CARBONATE • ALUMINA • DISODIUM EDTA • PHENOXYETHANOL • [+/- MICA • IRON OXIDES (CI 77491, CI 77492, CI 77499) • TITANIUM DIOXIDE (CI 77891) • CHROMIUM HYDROXIDE GREEN (CI 77289) • CHROMIUM OXIDE GREENS (CI 77288)]

WARNING

WHEN USING

Keep out of eyes.

Stop use if irritation occurs.

Keep out of reach of children.

PRINCIPAL DISPLAY PANEL - 30 ml Carton

ESTĒE LAUDER

Equalizer
Smart Makeup

SPF 10

1 FL. OZ. LIQ./30ml e